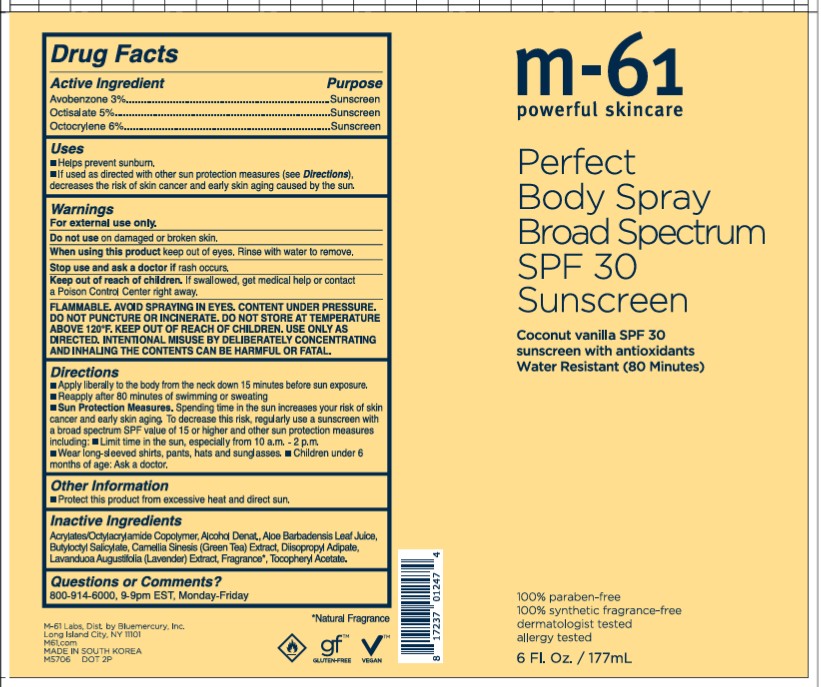 DRUG LABEL: m61 Perfect Body Broad Spectrum SPF 30 Sunscreen
NDC: 72203-022 | Form: AEROSOL, SPRAY
Manufacturer: Bluemercury
Category: otc | Type: HUMAN OTC DRUG LABEL
Date: 20250313

ACTIVE INGREDIENTS: OCTISALATE 5 g/100 mL; AVOBENZONE 3 g/100 mL; OCTOCRYLENE 6 g/100 mL
INACTIVE INGREDIENTS: BUTYLOCTYL SALICYLATE; ACRYLATES/OCTYLACRYLAMIDE COPOLYMER (40000 MW); ALOE BARBADENSIS LEAF JUICE; DIISOPROPYL ADIPATE; FRAGRANCE LAVENDER ORC1800979; ALPHA-TOCOPHEROL ACETATE; ALCOHOL; FRAGRANCE ESC 10-740; CAMELLIA SINENSIS LEAF

m-61 Perfect Body Spray Broad Spectrum 30 Sunscreen

Drug Facts

ACTIVE INGREDIENT

Active Ingredient | Purpose
Avobenzone (3%) | Sunscreen
Octisalate (5%) | Sunscreen
Octocrylene (6%) | Sunscreen

Uses

- Helps prevent sunburn.
- If used as directed with other sun protection measures (see Directions), decreases the risk of skin cancer and early skin aging caused by the sun.

WARNINGS

For external use only.

Do not use on damaged or broken skin.

When using this product keep out of eyes. Rinse with water to remove.

Stop use and ask a doctor if rash occurs.

Keep out of reach of children. If swallowed, get medical help or contact a Poison Control Center right away.

FLAMMABLE

FLAMMABLE. AVOID SPRAYING IN EYES. CONTENT UNDER PRESSURE. DO NOT PUNCTURE OR INCINERATE. DO NOT STORE AT TEMPERATURE ABOVE 120F. KEEP OUT OF REACH OF CHILDREN. USE ONLY AS DIRECTED. INTENTIONAL MISUSE BY DELIBERATELY CONCENTRATING AND INHALING THE CONTENTS CAN BE HARMFUL OR FATAL.

Directions

- Apply liberally to the body from the neck down 15 minutes before sun exposure.
- Reapply after 80 minutes of swimming or sweating.
- Sun protection Measures. Spending time in the sun increases your risk of skin cancer and early skin aging. To decrease this risk, regularly use a sunscreen with a broad spectrum SPF value of 15 or higher and other sun protection measures including:
- Limit time in the sun, especially from 10 a.m. - 2 p.m.
- Wear long-sleeved shirts, pants, hats and sunglasses.
- Children under 6 months of age: Ask a doctor.

OTHER SAFETY INFORMATION

- Protect this product from excessive heat and direct sun.

INACTIVE INGREDIENT

Acrylates/Octylacrylamide Copolymer, Alcohol Denat., Aloe Barbadensis Leaf Juice, Butyloctyl Salicylate, Camellia Sinesis (Green Tea) Extract, Diisopropyl Adipate, Lavanduoa Augustifolia (Lavender) Extract, Fragrance, Tocopheryl Acetate.

Questions or Comments?

800-914-6000, 9-9pm EST, Monday-Friday

m-61 Perfect Body Spray Broad Spectrum SPF 30 Sunscreen

m-61

powerful skincare

Perfect

Body Spray

Broad Spectrum

SPF 30

Sunscreen

Coconut vanilla SPF 30

sunscreen with antioxidants

Water Resistant (80 Minutes)

100% paraben-free

100% synthetic fragrance-free

dermatologist tested

allergy tested

6 Fl. Oz./177mL